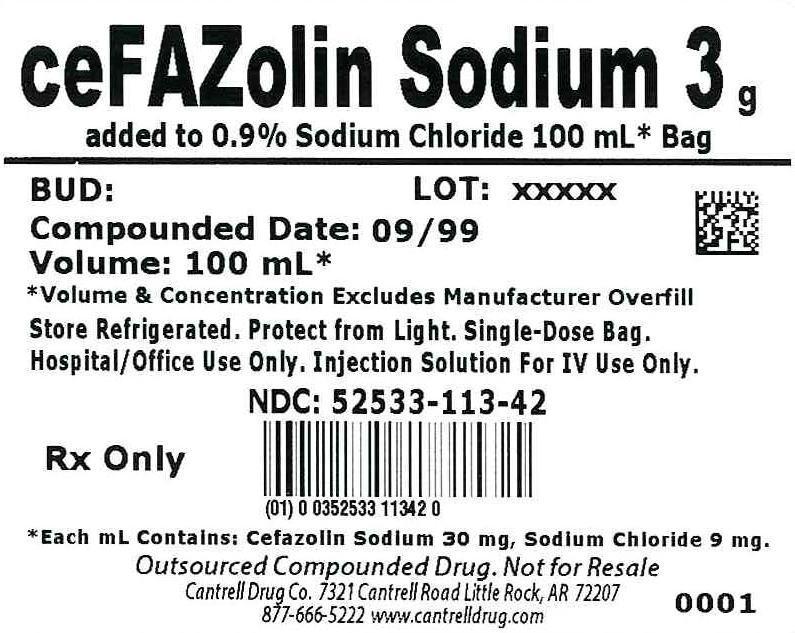 DRUG LABEL: Cefazolin Sodium
NDC: 52533-113 | Form: INJECTION, SOLUTION
Manufacturer: Cantrell Drug Company
Category: prescription | Type: HUMAN PRESCRIPTION DRUG LABEL
Date: 20140602

ACTIVE INGREDIENTS: Cefazolin Sodium 30 mg/1 mL
INACTIVE INGREDIENTS: Sodium Chloride 9 mg/1 mL; Water

Cefazolin Sodium 3 g Added to 0.9% Sodium Chloride 100 mL Bag